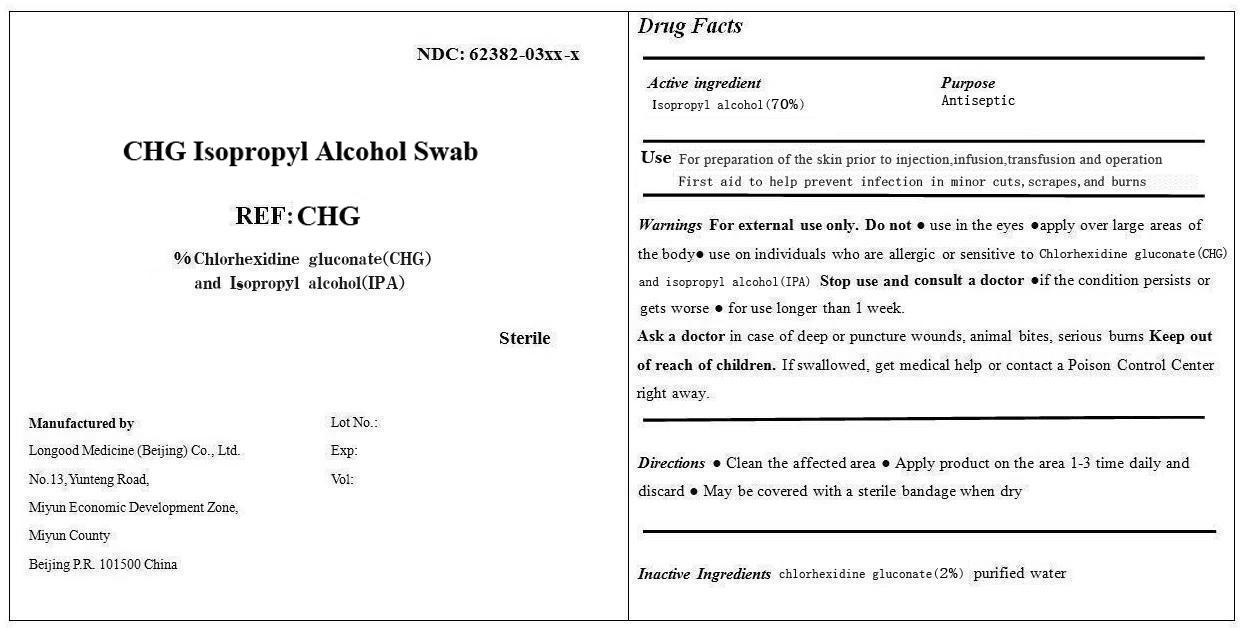 DRUG LABEL: CHG
NDC: 62382-0324 | Form: SWAB
Manufacturer: Longood Medicine (Beijing) Co., Ltd.
Category: otc | Type: HUMAN OTC DRUG LABEL
Date: 20201226

ACTIVE INGREDIENTS: ISOPROPYL ALCOHOL 0.7 mL/1 mL
INACTIVE INGREDIENTS: WATER; CHLORHEXIDINE GLUCONATE

Drug Fact

Active Ingredient

Isopropyl Alcohol 70%

Purpose

Antiseptic

Use

For preparation of the skin prior to injection, infusion, transfusion, and operation.

First aid to help prevent infection in minor cut, scrapes, abd burns

Warning

For external use only.

Do Not Use

Do not

● use in the eyes

● use on individuals who are allergic or sensitive to Chlorhexidine gluconate (CHG) and isopropyl alcohol (IPA)

Stop Use and Consult a Doctor

●if the condition persists or gets worse

● for use longer than 1 week. Ask a doctor in case of deep or puncture wounds, animal bites, serious burns

Ask a doctor in case of deep or puncture wounds, animal bites, serious burns

Keep out of reach of children

If swallowed, get medical help or contact a Poison Control Center right away.

Direction:

Directions

- Clean the affected area
- Apply the product to the area 1-3 times daily and discard.
- Maybe coverd with a sterile bandage when dry

Inactive Ingredient

Chlorhexidine Glutanate (2%), Purified water